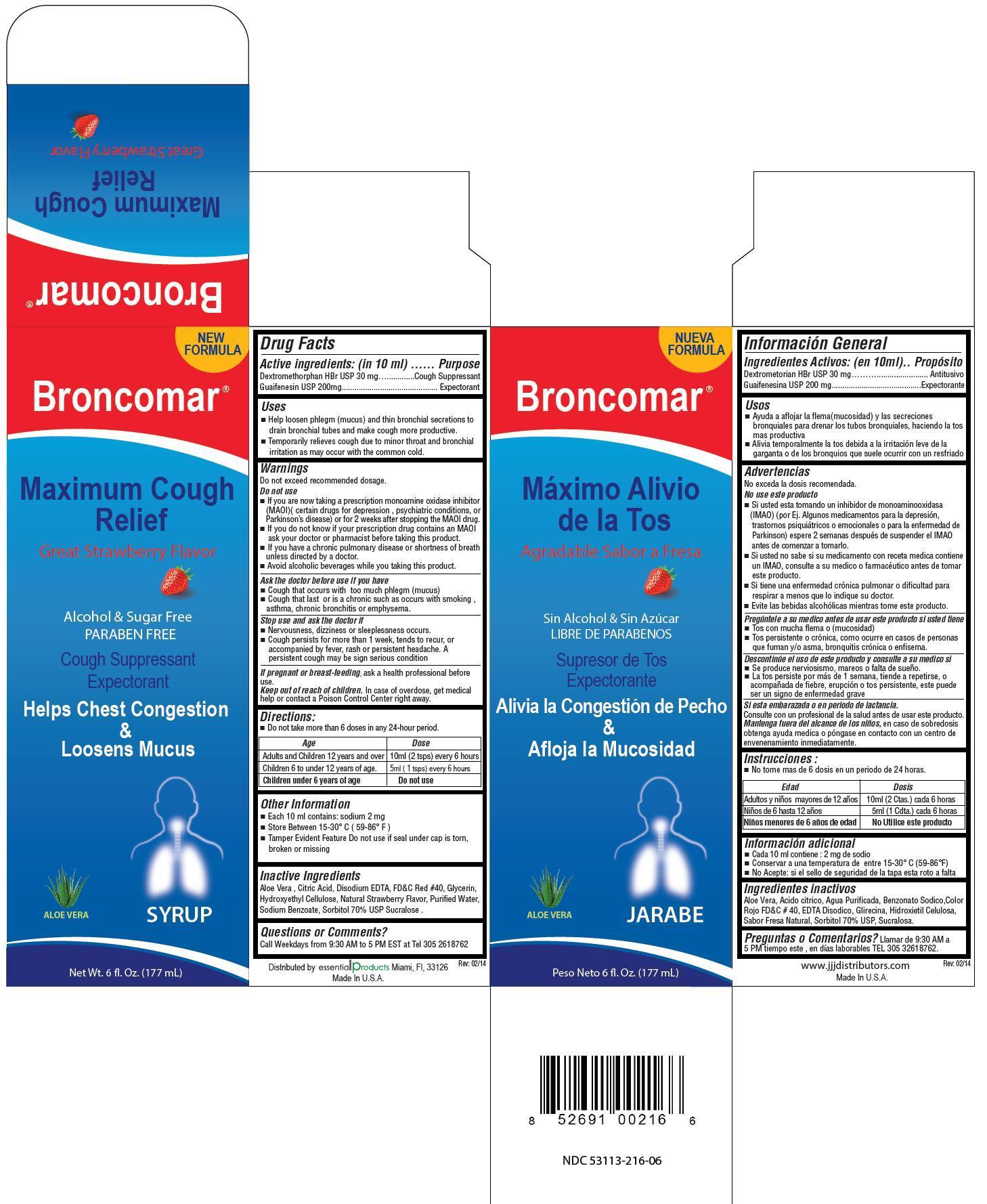 DRUG LABEL: Broncomar
NDC: 53113-216 | Form: LIQUID
Manufacturer: Gadal Laboratories Inc
Category: otc | Type: HUMAN OTC DRUG LABEL
Date: 20140612

ACTIVE INGREDIENTS: DEXTROMETHORPHAN HYDROBROMIDE 30 mg/10 mL; GUAIFENESIN 200 mg/10 mL
INACTIVE INGREDIENTS: ALOE VERA WHOLE; ANHYDROUS CITRIC ACID; EDETATE DISODIUM; FD&C RED NO. 40; GLYCERIN; HYDROXYMETHYL CELLULOSE; WATER; SODIUM BENZOATE; SORBITOL; SUCRALOSE

ACTIVE INGREDIENT

Acvtive ingredients: (in 10 ml) Purpose

Dextromethorphan HBr 30 mg ................... Cough Suppressant

Guaifenesin 200 mg ................................... Expectorant

Purpose

Cough Suppressant

Expectorant

Uses

- Help loosen phlegm (mucus) and thin bronchial secretions to drain bronchial tubes and make cough more productive.
- Teporarily relieves cough due to minor throat and bronchial irritation as may occur with the common cold

Warnings

Do not exceed recommended dosage

Do not use

- If you are now taking a prescription monoamine oxidase inhibitor (MAOI)(certain drugs for depression , psychiatric conditions, or Parkinson’s disease) or for 2 weeks after stopping the MAOI drug.
- if you do not know if your prescription drug contains on MAOI ask your doctor or pharmacist before taking this product
- if you have a chronic pulmonary disease or shortness of breath unless directed by a doctor
- avoid alcoholic beverages while you are taking this product

Ask the doctor before use if you have

- cough that occurs with too much phlegm (mucus)
- cough that lasts or is chronic such as occurs with smoking, asthma, chronic bronchitis or emphysema

Stop use and ask the doctor if

- Nervoisness, dizziness or sleeplessness occurs.
- Cough persists for more than 1 week, tends to recur, or accompanied by fever, rash or persistent headache. A persistent cough may be sign of a serious condition

PREGNANCY OR BREAST FEEDING

If pregnant or breast-feeding, ask a health professional before use.

Keep out of reach of children. In case of overdose, get medical help or contact a Poison Control Center right away.

Directions

- Do not take more than 6 doses in any 24-hour period

Age Dose

Adults and children 12 years and over 10 mL (2 tsps) every 4 hours

Children 6 to under 12 years of age. 5 mL (1 tsps) every 4 hours

Children under 6 years of age Do not use

Inactive ingredients

Aloe vera, citric acid, disodium EDTA, FD&C Red #40, glycerin, hydroxyethyl cellulose, natural strawberry flavor, water, sodium benzoate, sorbitol 70%, sucralose